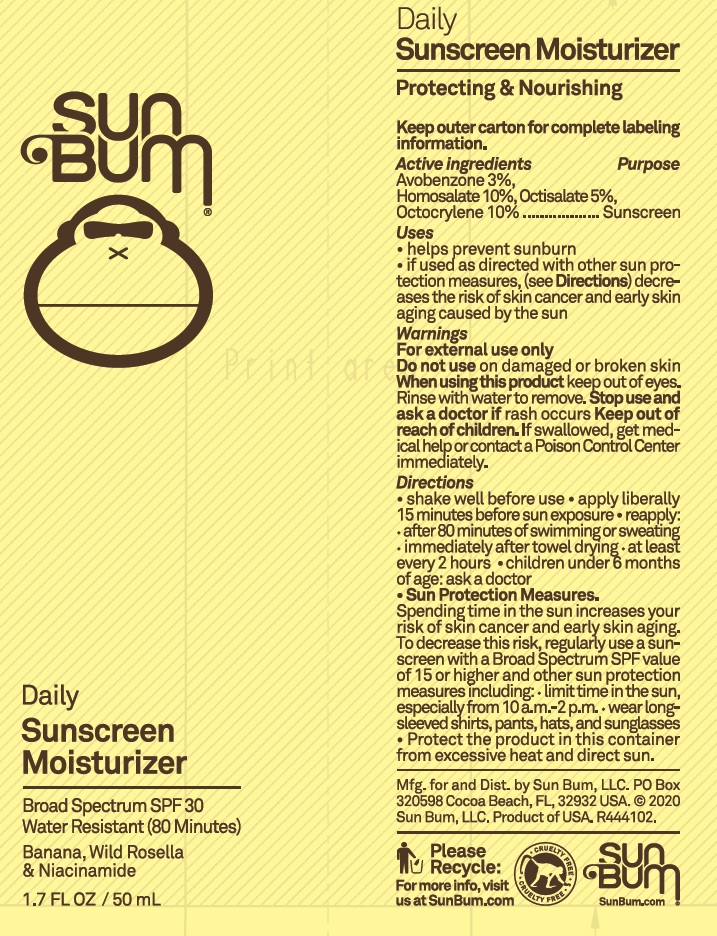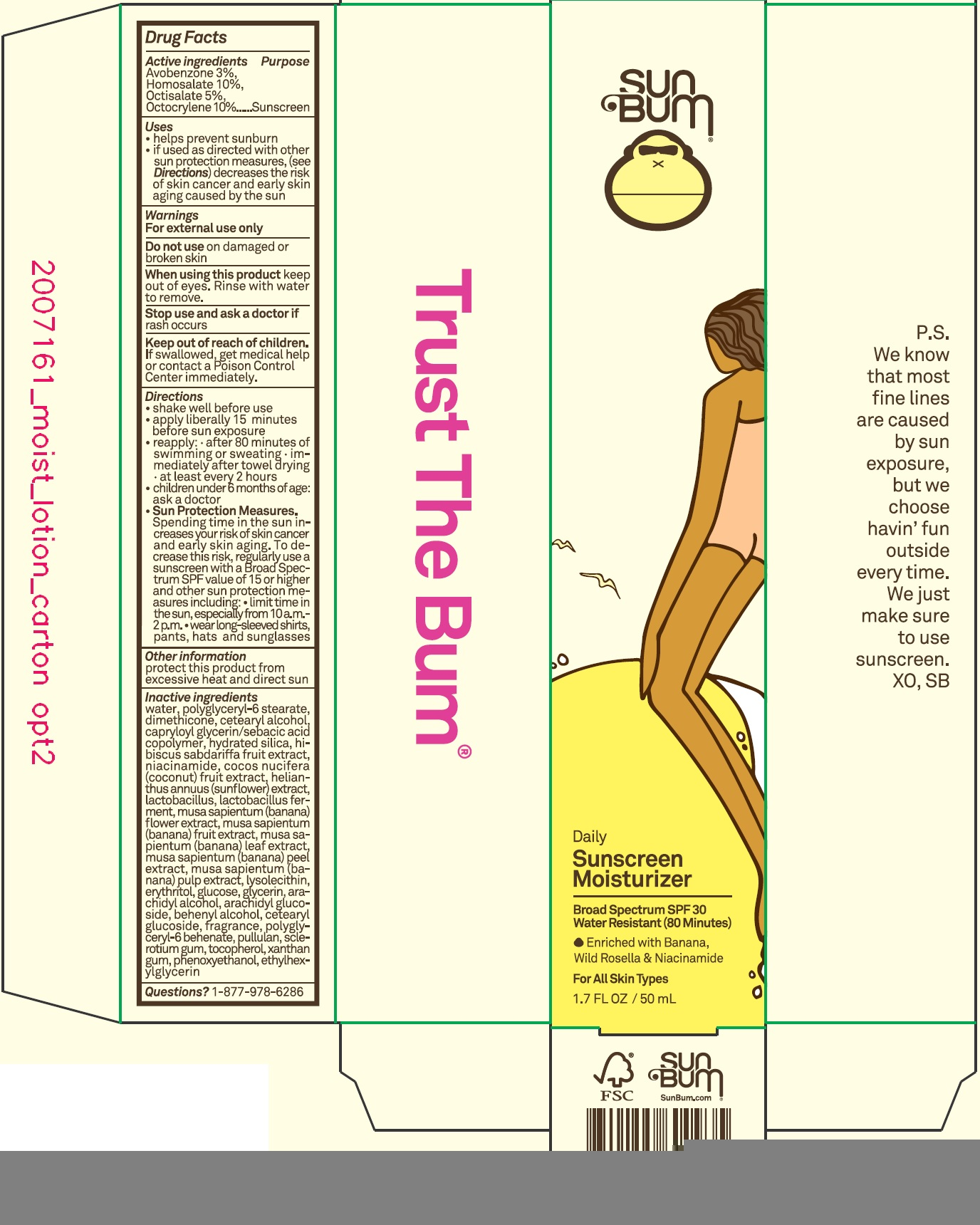 DRUG LABEL: Sun bum Daily Sunscreen Moisturizer SPF 30
NDC: 69039-625 | Form: LOTION
Manufacturer: Sun Bum LLC
Category: otc | Type: HUMAN OTC DRUG LABEL
Date: 20220204

ACTIVE INGREDIENTS: AVOBENZONE 30 mg/1 mL; HOMOSALATE 100 mg/1 mL; OCTISALATE 50 mg/1 mL; OCTOCRYLENE 100 mg/1 mL
INACTIVE INGREDIENTS: WATER; POLYGLYCERYL-6 STEARATE; DIMETHICONE; CETOSTEARYL ALCOHOL; CAPRYLOYL GLYCERIN/SEBACIC ACID COPOLYMER (2000 MPA.S); HYDRATED SILICA; NIACINAMIDE; COCONUT; HELIANTHUS ANNUUS FLOWERING TOP; MUSA X PARADISIACA FLOWER; BANANA; MUSA X PARADISIACA LEAF; BANANA PEEL; LYSOPHOSPHATIDYLCHOLINE, SOYBEAN; ERYTHRITOL; ANHYDROUS DEXTROSE; GLYCERIN; ARACHIDYL ALCOHOL; ARACHIDYL GLUCOSIDE; DOCOSANOL; CETEARYL GLUCOSIDE; POLYGLYCERYL-6 BEHENATE; PULLULAN; BETASIZOFIRAN; TOCOPHEROL; XANTHAN GUM; PHENOXYETHANOL; ETHYLHEXYLGLYCERIN

Sun bum Daily Sunscreen Moisturizer SPF 30

Active ingredients

Avobenzone 3%,

Homosalate 10%,

Octisalate 5%,

Octocrylene 10%

Purpose

Sunscreen

Uses

- helps prevent sunburn
- if used as directed with other sun protection measures, (see Directions) decreases the risk of skin cancer and early skin aging caused by the sun

Warnings

For external use only

Do not use

on damaged or broken skin

When using this product

keep out of eyes. Rinse with water to remove.

Stop use and ask a doctor if

rash occurs

Keep out of reach of children.

If swallowed, get medical help or contact a Poison Control Center immediately.

Directions

- shake well before use
- apply liberally 15 minutes before sun exposure
- reapply: after 80 minutes of swimming or sweating immediately after towel drying at least every 2 hours
- children under 6 months of age: ask a doctor

Sun Protection Measures. Spending time in the sun increases your risk of skin cancer and early skin aging. To decrease this risk, regularly use a sunscreen with a Broad Spectrum SPF value of 15 or higher and other sun protection measures including:

- limit time in the sun, especially from 10 a.m.-2 p.m.
- wear long-sleeved shirts, pants, hats and sunglasses

Other information

protect this product from excessive heat and direct sun

Inactive ingredients

water, polyglyceryl-6 stearate, dimethicone, cetearyl alcohol, capryloyl glycerin/sebacic acid copolymer, hydrated silica, hibiscus sabdariffa fruit extract, niacinamide, cocos nucifera (coconut) fruit extract, helianthus annuus (sunflower) extract, lactobacillus, lactobacillus ferment, musa sapientum (banana) flower extract, musa sapientum (banana) fruit extract, musa sapientum (banana) leaf extract, musa sapientum (banana) peel extract, musa sapientum (banana) pulp extract, lysolecithin, erythritol, glucose, glycerin, arachidyl alcohol, arachidyl glucoside, behenyl alcohol, cetearyl glucoside, fragrance, polyglyceryl-6 behenate, pullulan, sclerotium gum, tocopherol, xanthan gum, phenoxyethanol, ethylhexylglycerin

Questions?

1-877-978-6286